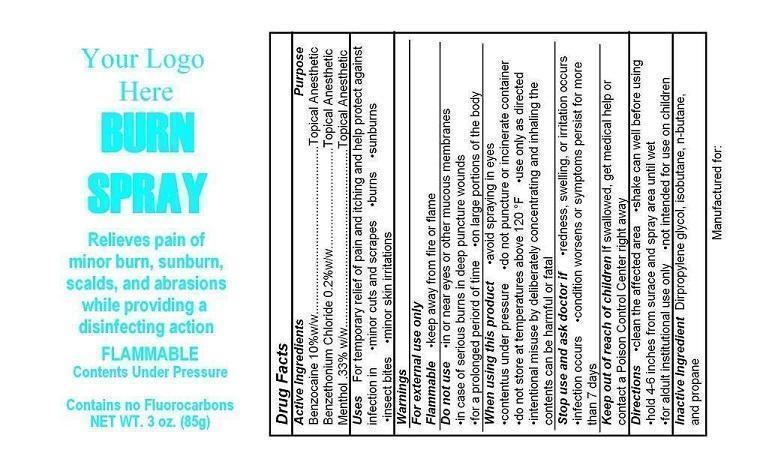 DRUG LABEL: Your Logo Here Burn First Aid
NDC: 52982-101 | Form: AEROSOL, SPRAY
Manufacturer: Dixon Investments, Inc.
Category: otc | Type: HUMAN OTC DRUG LABEL
Date: 20250128

ACTIVE INGREDIENTS: BENZOCAINE 8500 mg/85 g; BENZETHONIUM CHLORIDE 170 mg/85 g; MENTHOL 281 mg/85 g
INACTIVE INGREDIENTS: DIPROPYLENE GLYCOL; ISOBUTANE; BUTANE; PROPANE

YOUR LOGO HERE BURN SPRAY

Active Ingredients

Benzocaine 10% w/w
Benzethonium Chloride .2% w/w
Menthol .33% w/w

Purpose

Topical Anesthetic
Topical Anesthetic
Topical Anesthetic

Uses

For temporary relief of pain and ithcing and help protect against infection in
minor cuts and scrapes
burns
sunburnsinsect bitesminor skin irritations

Warnings

For external use only

Flammable

keep away from fire or flame

Do not use

in or near eyes or other mucous membranes
in case of serious burns in deep puncture wounds
for a prolonged period of time
on large portions of the body

When using this product

avoid spraying in eyes
contents under pressuredo not puncture or incinerate containerdo not store at temperatures above 120°(F)use only as directedintentional misuse by deliberately concentrating and inhaling the contents can be harmful or fatal

Stop use and ask doctor if

redness, swelling, or irritation occurs
infection occurs
conditions worsens or symptoms persist for more than 7 days

Keep out of reach of children

If swallowed, get medical help or contact a Poison Control Center right away

Directions

clean the affected area
shake can well before using
hold 4-6 inches from surface and spray area until wet
for adult institutional use only
not intended for use on children

Inactive Ingredient

Dipropylene glycol, isobutane, n-butane, and propane